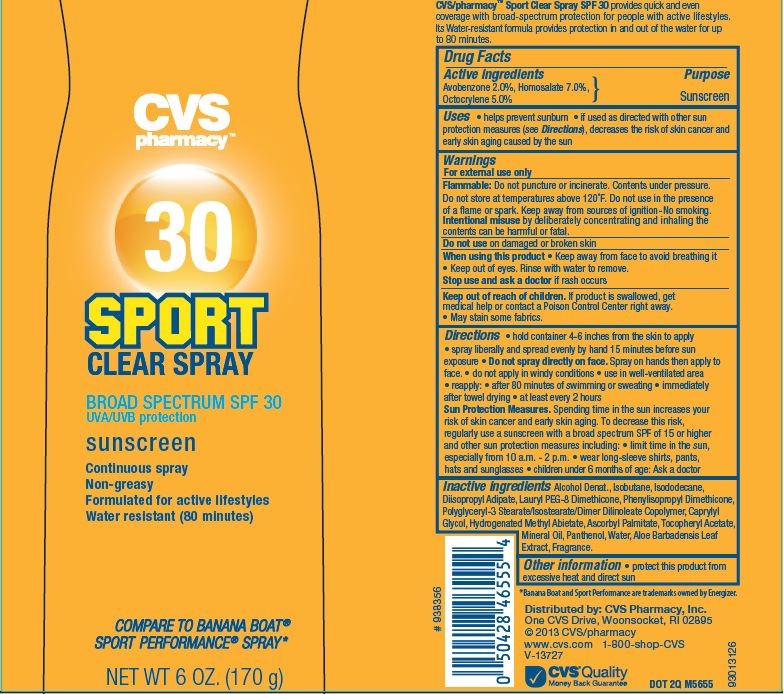 DRUG LABEL: CVS
NDC: 59779-674 | Form: SPRAY
Manufacturer: CVS Pharmacy
Category: otc | Type: HUMAN OTC DRUG LABEL
Date: 20151020

ACTIVE INGREDIENTS: AVOBENZONE 2 g/100 g; HOMOSALATE 7 g/100 g; OCTOCRYLENE 5 g/100 g
INACTIVE INGREDIENTS: .ALPHA.-TOCOPHEROL ACETATE; MINERAL OIL; PANTHENOL; WATER; ALOE VERA LEAF; ALCOHOL; ISOBUTANE; ISODODECANE; DIISOPROPYL ADIPATE; CAPRYLYL GLYCOL; HYDROGENATED METHYL ABIETATE; ASCORBYL PALMITATE

Drug Facts

Active ingredients

Avobenzone 2.0%, Homosalate 7.0%, Octocrylene 5.0%

Purpose

Sunscreen

Uses

- helps prevent sunburn
- if used as directed with other sun protection measures (see Directions), decreases the risk of skin cancer and early skin aging caused by the sun

Warnings

For external use only

Flammable

Do not puncture or incinerate. Contents under pressure. Do not store at temperatures above 120^0 F. Do not use in the presence of a flame or spark. Keep away from sources of ignition-No smoking.

Intentional misuse by deliberately concentrating and inhaling the contents can be harmful or fatal.

Do not use

on damaged or broken skin

When using this product

- Keep away from face to avoid breathing it

- Keep out of eyes. Rinse with water to remove

Stop use and ask a doctor

if rash occurs

Keep out of reach of children

If a product is swallowed, get medical help or contact a Poison Control Center right away.

- May stain some fabrics.

Directions

- hold container 4-6 inches from the skin to apply
- spray liberally and spread evenly by hand 15 minutes before sun exposure
- Do not spray directly on face. Spray on hands then apply to face.
- do not apply in windy conditions
- use in well-ventilated area
- reapply:
- after 80 minutes of swimming or sweating
- immediately after towel drying
- at least every 2 hours

Sun Protection Measures. Spending time in the sun increases your risk of skin cancer and early skin aging. To decrease this risk, regularly use a sunscreen with a broad spectrum SPF of 15 or higher and other sun protection measures including:

- limit time in the sun, especially from 10 a.m.-2p.m.
- wear long-sleeve shirts, pants, hats and sunglasses
- children under 6 months of age: Ask a doctor.

Inactive Ingredients

Alcohol Denat., Isobutane, Isododecane, Diisopropyl Adipate, Lauryl PEG-8 Dimethicone, Phenylisopropyl Dimethicone, Polyglyceryl-3 Stearate/Isostearate/Dimer Dilinoleate Copolymer, Caprylyl Glycol, Methyl Dihydroabietate, Fragrance, Ascorbyl Palmitate, Tocopheryl Acetate, Mineral Oil, Panthenol, Water, Aloe Barbadensis Leaf Extract.

Other information

- protect this product from excessive heat and direct sun

Principal Display Panel

CVS

pharmacy

30

SPORT

CLEAR SPRAY

BROAD SPECTRUM SPF 30

UVA/UVB protection

sunscreen

Continuous spray

Non-greasy

Formulated for active lifestyles

Water resistant (80 minutes)

COMPARE TO BANANA BOAT

SPORT PERFORMANCE SPRAY

NET WT 6 OZ. (170 g)